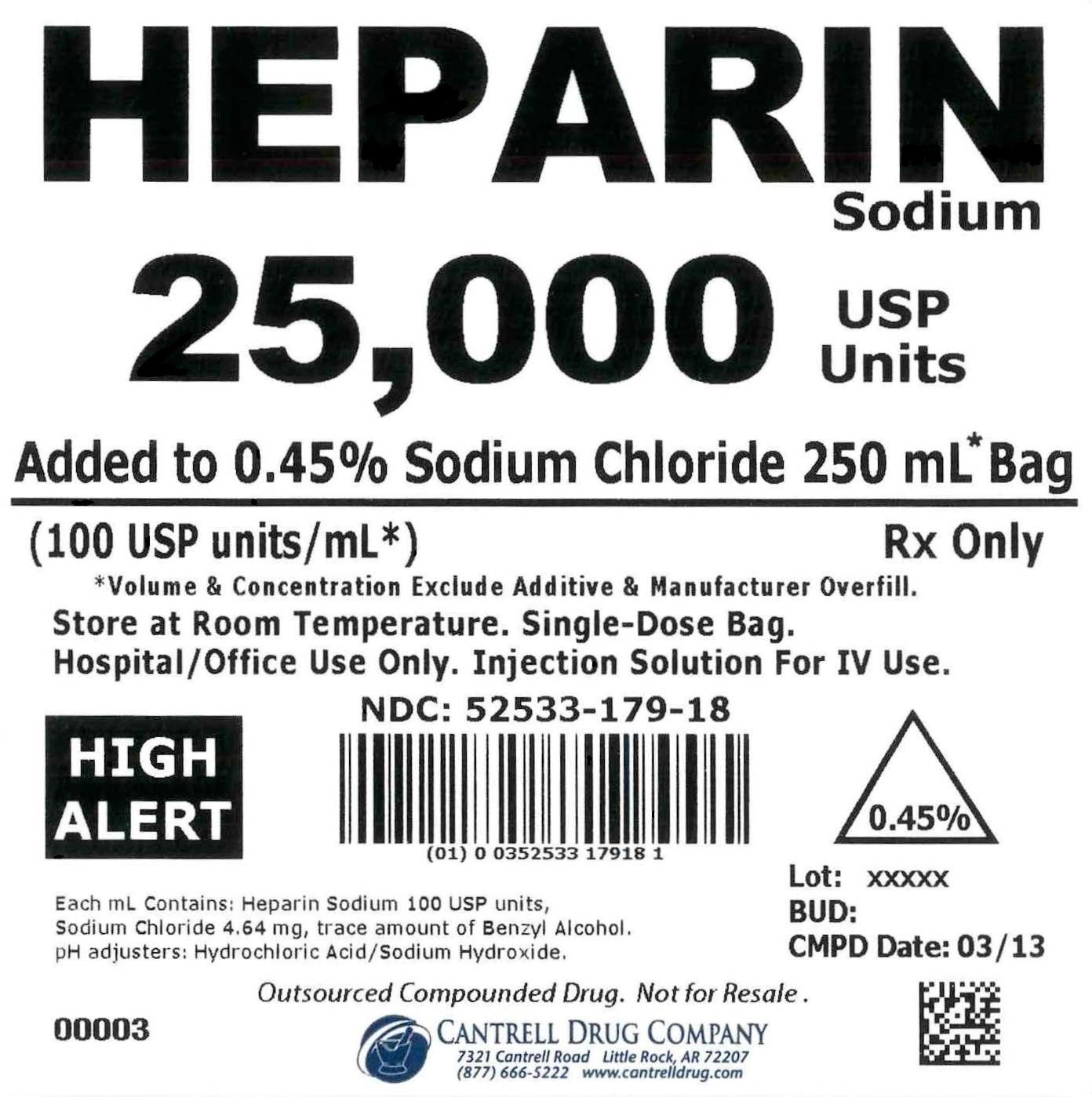 DRUG LABEL: Heparin Sodium
NDC: 52533-179 | Form: INJECTION, SOLUTION
Manufacturer: Cantrell Drug Company
Category: prescription | Type: HUMAN PRESCRIPTION DRUG LABEL
Date: 20150515

ACTIVE INGREDIENTS: Heparin Sodium 100 [USP'U]/1 mL
INACTIVE INGREDIENTS: Sodium Chloride 4.5 mg/1 mL; BENZYL ALCOHOL 0.0002 mL/1 mL; Water

Heparin Sodium 25,000 USP Units Added to 0.45% Sodium Chloride 250 mL Bag

• WARNINGS AND PRECAUTIONS

Outsourced Compounded Drug. Not for Resale. Hospital/Office Use Only.

• ADVERSE EVENTS

To facilitate Adverse Event Reporting: www.fda.gov/medwatch or 1-800-FDA-1088.

• HOW SUPPLIED

Contains 25,000 USP Units of Heparin Sodium in 0.45% Sodium Chloride in a 250 mL Single-Dose Bag. Volume & Concentration exlude additive & manufacturer overfill.

This product is Sterile, Nonpyrogenic, and Latex Free.

• INGREDIENTS

Each 1 mL contains contains Heparin Sodium 100 USP Units, Sodium Chloride 4.5 mg, Benzyl Alcohol 0.0002 mL. May contain Hydrochloric Acid and/or Sodium Hydroxide for pH adjustment.

• STORAGE AND HANDLING

Store at 20° to 25°C (68° to 77°F). [See USP Controlled Room Temperature].

• DOSAGE AND ADMINISTRATION.

FOR INTRAVENOUS USE.

Rx Only

Rev. 05/15

CANTRELL DRUG COMPANY

LITTLE ROCK, AR 72207